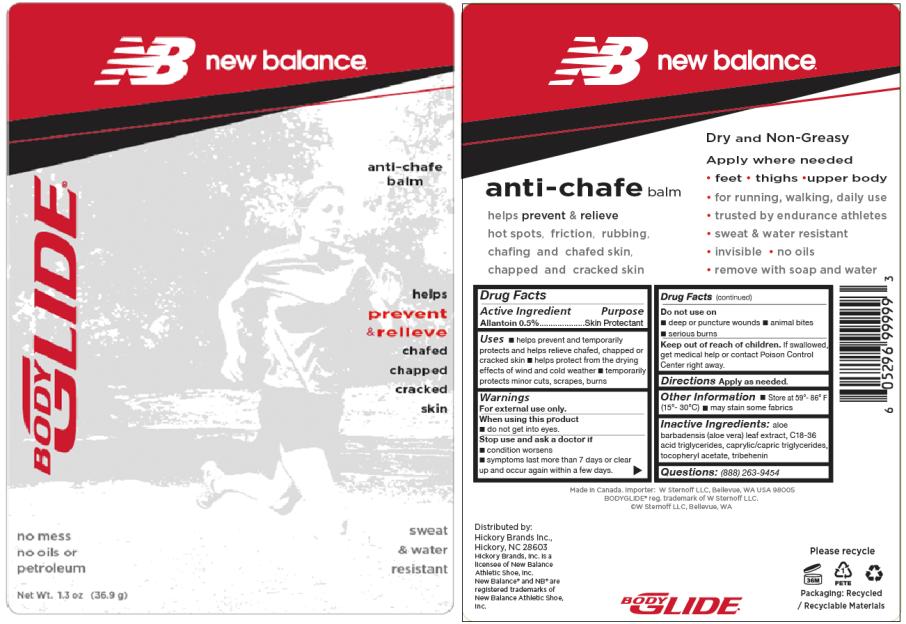 DRUG LABEL: Anti Chafe Balm
NDC: 52342-001 | Form: STICK
Manufacturer: Hickory Brands Inc.
Category: otc | Type: HUMAN OTC DRUG LABEL
Date: 20100606

ACTIVE INGREDIENTS: ALLANTOIN 5 mg/1 g
INACTIVE INGREDIENTS: ALOE VERA LEAF; MEDIUM-CHAIN TRIGLYCERIDES; .ALPHA.-TOCOPHEROL ACETATE, D-; TRIBEHENIN

Anti-Chafe Balm

Drug Facts

Active Ingredient:

Allantoin 0.5%

Purpose:

Skin Protectant

Uses:

- helps prevent and temporarily protects and helps relieve chafed, chapped or cracked skin
- helps protect from the drying effects of wind and cold weather
- temporarily protects minor cuts, scrapes, burns

Warnings

For external use only.

When using this product

- do not get into eyes

Stop use and ask a doctor if

- condition worsens
- symptoms last more than 7 days or clear up and occur again within a few days

Do not use on

- deep or puncture wounds
- animal bites
- serious burns

Keep out of reach of children.

If swallowed, get medical help or contact Poison Control Center right away.

Directions

Apply as needed.

Other Information

- Store at 59º – 86º F (15º - 30º C)
- may stain some fabrics

Inactive Ingredients:

aloe barbadensis (aloe vera) leaf juice, C18-36 acid triglycerides, caprylic/capric triglycerides, tocopheryl acetate, tribehenin

Questions:

(888) 263-9454

Principal Display Panel

NB new balance.
anti-chafe
balm
BodyGlide®
helps
prevent
& relieve
chafed
chapped
cracked
skin
no mess
no oils or
petroleum
sweat
& water
resistant
Net Wt. 1.3 oz (36.9 g)